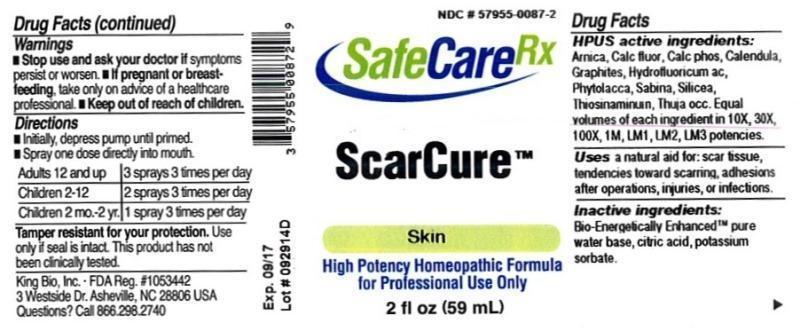 DRUG LABEL: ScarCure
NDC: 57955-0087 | Form: LIQUID
Manufacturer: King Bio Inc.
Category: homeopathic | Type: HUMAN OTC DRUG LABEL
Date: 20150319

ACTIVE INGREDIENTS: ARNICA MONTANA 10 [hp_X]/59 mL; CALCIUM FLUORIDE 10 [hp_X]/59 mL; TRIBASIC CALCIUM PHOSPHATE 10 [hp_X]/59 mL; CALENDULA OFFICINALIS FLOWERING TOP 10 [hp_X]/59 mL; GRAPHITE 10 [hp_X]/59 mL; HYDROFLUORIC ACID 10 [hp_X]/59 mL; PHYTOLACCA AMERICANA ROOT 10 [hp_X]/59 mL; JUNIPERUS SABINA LEAFY TWIG 10 [hp_X]/59 mL; SILICON DIOXIDE 10 [hp_X]/59 mL; ALLYLTHIOUREA 10 [hp_X]/59 mL; THUJA OCCIDENTALIS LEAFY TWIG 10 [hp_X]/59 mL
INACTIVE INGREDIENTS: WATER; ANHYDROUS CITRIC ACID; POTASSIUM SORBATE

ScarCure™

ACTIVE INGREDIENT

Drug Facts__________________________________________________________________________________________________________

HPUS active ingredients: Arnica montana, Calcarea fluorica, Calcarea phosphorica, Calendula officinalis, Graphites, Hydrofluoricum acidum, Phytolacca decandra, Sabina, Silicea, Thiosinaminum, Thuja occidentalis. Equal volumes of each ingredient in 10X, 30X, 100X, 1M, LM1, LM2, LM3 potencies.

INDICATIONS AND USAGE

Uses a natural aid for: scar tissue, tendencies toward scarring, adhesions after operations, injuries, or infections.

Inactive Ingredients:

Bio-Energetically Enhanced™ pure water, citric acid and potassium sorbate.

Warnings

- Stop use and ask your doctor if symptoms persist or worsen.
- If pregnant or breast-feeding, take only on advice of a healthcare professional.

- Keep out of reach of children.

Directions

- Initially, depress pump until primed.
- Spray one dose directly into mouth.
- Adults 12 and up: 3 sprays 3 times per day
- Children 2-12: 2 sprays 3 times per day
- Children 2 mo-2 yr. 1 spray 3 times per day

OTHER SAFETY INFORMATION

Tamper resistant for your protection. Use only if safety seal is intact. This product has not been clinically tested.

PURPOSE

Uses a natural aid for:

- scar tissue
- tendencies toward scarring
- adhesions after operations, injuries, or infections